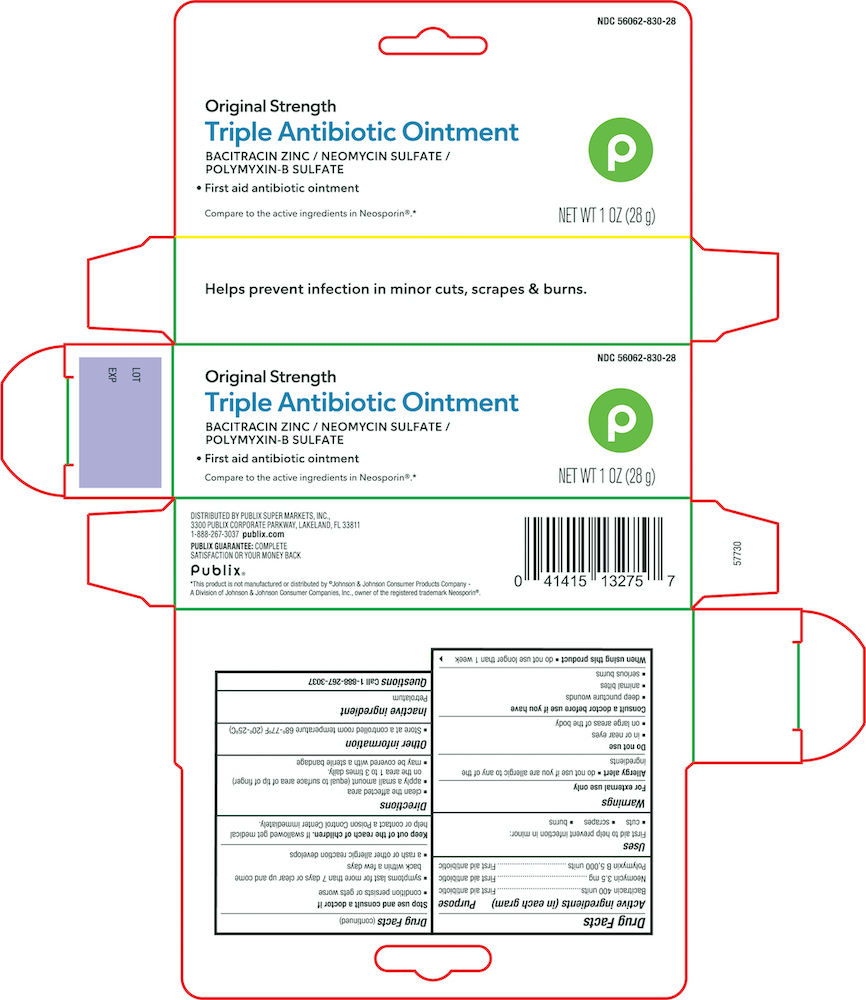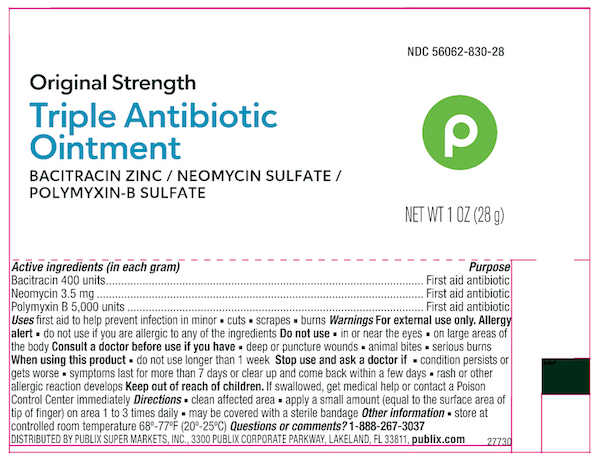 DRUG LABEL: Publix Triple Antibiotic
NDC: 56062-830 | Form: OINTMENT
Manufacturer: PUBLIX SUPER MARKETS, INC.
Category: otc | Type: HUMAN OTC DRUG LABEL
Date: 20240617

ACTIVE INGREDIENTS: BACITRACIN ZINC 400 [USP'U]/1 g; POLYMYXIN B SULFATE 5000 [USP'U]/1 g; NEOMYCIN SULFATE 3.5 mg/1 g
INACTIVE INGREDIENTS: PETROLATUM

Publix Triple Antibiotic Ointment

Active ingredient

Bacitracin 400 units

Neomycin 3.5 mg/g

Polymyxin B 5000 units

Purpose

Bacitracin 400 units..........First aid antibiotic

Neomycin 3.5 mg/g..........First aid antibiotic

Polymyxin B 5000 units....First aid antibiotic

Uses

First aid to help prevent infection in minor;

- cuts
- scrapes
- burns

Warnings

For external use only

Allergy alert

- do not use if you are allergic to any of the ingredients

Do not use

- in or near eyes
- on large area of the body

Consult a doctor before use if you have

- deep puncture wounds
- animal bites
- serious burns

When using this product

do not use longer than 1 week

KEEP OUT OF REACH OF CHILDREN

Keep out of the reach of children. If swallowed get medical help or contact a Poison Control Center immediately.

Directions

- clean the affected area
- apply a small amount (equal to surface area of tip of finger) on the area 1 to 3 times daily.
- may be covered with a sterile bandage

Other information

Store at a controlled room temperature 20º-25ºC (68º-77ºF)

Inactive ingredient

Petrolatum

Principal Display Panel

Publix Triple Antibiotic Ointment NDC 56062-830-28

Bacitracin Zinc/ Neomycin Sulfate/ Polymyxin B Sulfate

NET WT 1.0 OZ (28g)